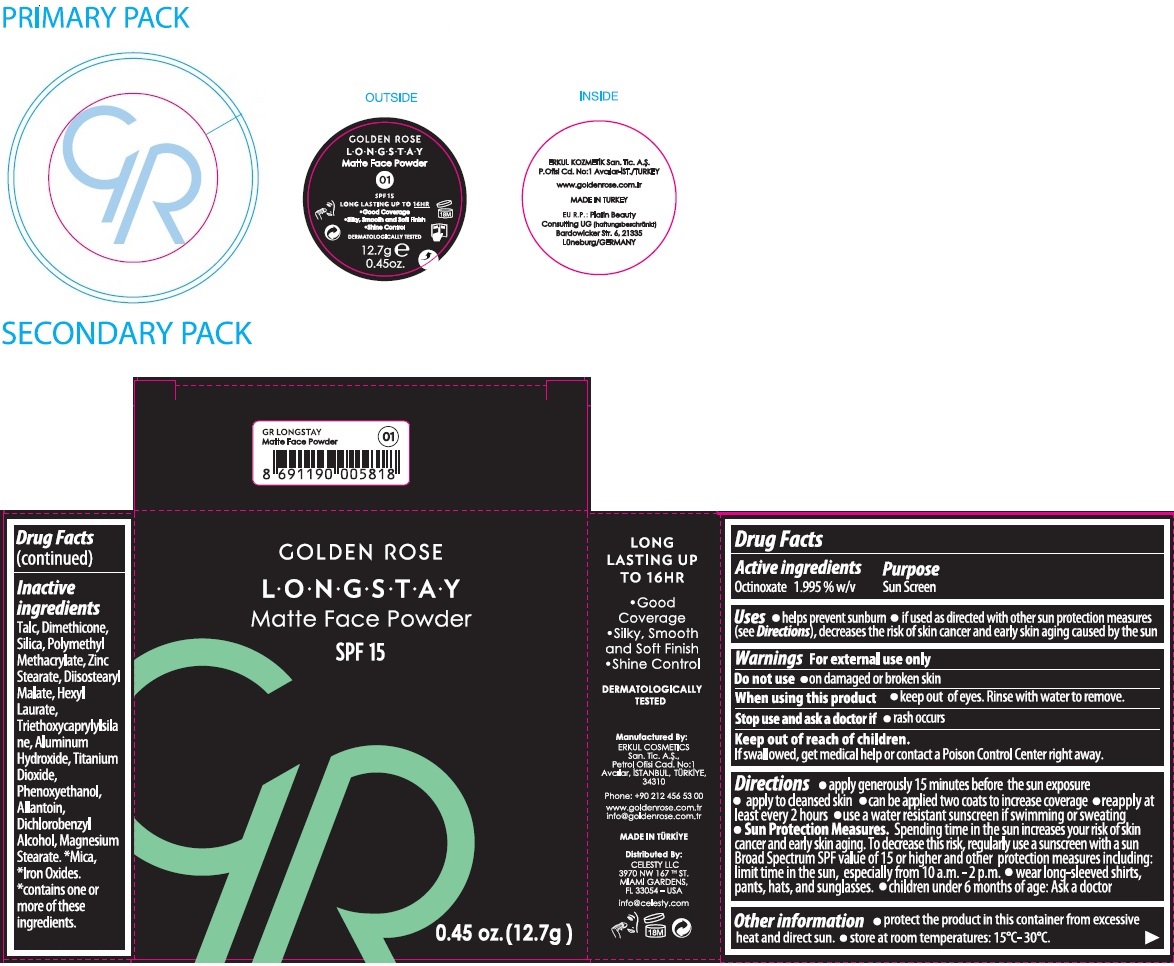 DRUG LABEL: GR LONGSTAY Matte Face Powder SPF 15
NDC: 82715-107 | Form: POWDER
Manufacturer: ERKUL KOZMETIK SANAYI VE TICARET ANONIM SIRKETI
Category: otc | Type: HUMAN OTC DRUG LABEL
Date: 20250807

ACTIVE INGREDIENTS: OCTINOXATE 1.995 g/100 g
INACTIVE INGREDIENTS: TALC; DIMETHICONE, UNSPECIFIED; SILICON DIOXIDE; POLY(METHYL METHACRYLATE; 450000 MW); ZINC STEARATE; DIISOSTEARYL MALATE; HEXYL LAURATE; TRIETHOXYCAPRYLYLSILANE; ALUMINUM HYDROXIDE; TITANIUM DIOXIDE; PHENOXYETHANOL; ALLANTOIN; DICHLOROBENZYL ALCOHOL; MAGNESIUM STEARATE; MICA; FERRIC OXIDE RED; FERRIC OXIDE YELLOW; FERROSOFERRIC OXIDE

GR GOLDEN ROSE LONGSTAY Matte Face Powder

Active ingredients

Octinoxate 1.995% w/v

Purpose

Sun Screen

Uses

• helps prevent sunburn • if used as directed with other sun protection measures (see Directions), decreases the risk of skin cancer and early skin aging caused by the sun

Warnings

For external use only

Do not use • on damaged or broken skin

When using this product • keep out of eyes. Rinse with water to remove.

Stop use and ask a doctor if • rash occurs

Keep out of reach of children.
If swallowed, get medical help or contact a Poison Control Center right away.

Directions

• apply generously 15 minutes before the sun exposure • apply to cleansed skin • can be applied two coats to increase coverage • reapply at least every 2 hours • use a water resistant sunscreen if swimming or sweating • Sun Protection Measures. Spending time in the sun increases your risk of skin cancer and early skin aging. To decrease this risk, regularly use a sunscreen with a sun Broad Spectrum SPF value of 15 or higher and other protection measures including: limit time in the sun, especially from 10 a.m. - 2 p.m. • wear long-sleeved shirts, pants, hats, and sunglasses. • children under 6 months of age: Ask a doctor

Other information

• protect the product in this container from excessive heat and direct sun. • store at room temperatures: 15°C- 30°C.

Inactive ingredients

Talc, Dimethicone, Silica, Polymethyl Methacrylate, Zinc Stearate, Diisostearyl Malate, Hexyl Laurate, Triethoxycaprylylsilane, Aluminum Hydroxide, Titanium Dioxide, Phenoxyethanol, Allantoin, Dichlorobenzyl Alcohol, Magnesium Stearate, *Mica, *Iron Oxodes. *contains one or more of these ingredients.

SPF 15

LONG LASTING UP TO 16HR

• Good Coverage
• Silky, Smooth and Soft Finish
• Shine Control

DERMATOLOGICALLY TESTED

Manufactured By:
ERKUL COSMETICS San. Tic. A.Ş.,
Petrol Ofisi Cad. No:1
Avcılar, ISTANBUL, TURKIYE,
34310

Phone: +90 212 456 53 00

www.goldenrose.com.tr
info@goldenrose.com.tr

MADE IN TURKIYE

Distributed By:
CELESTY LLC
3970 NW 167TH ST.
MIAMI GARDENS,
FL 33054 – USA

info@celesty.com

EU R.P: Platin Beauty Consulting UG
(haftungsbeschränkt)
Bardowicker Str. 6, 21335
Lüneburg/GERMANY